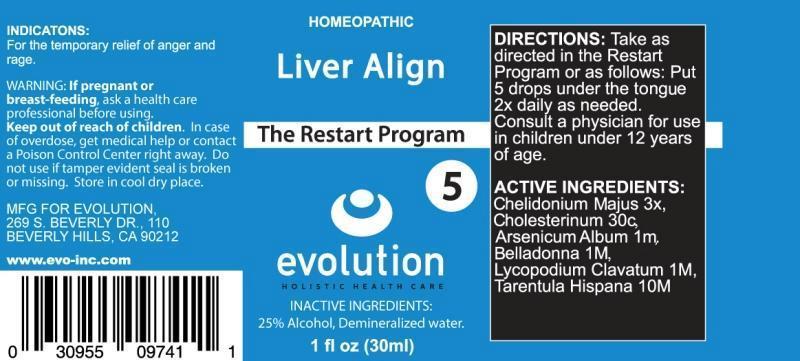 DRUG LABEL: LIVER ALIGN
NDC: 69414-0001 | Form: LIQUID
Manufacturer: Evolution
Category: homeopathic | Type: HUMAN OTC DRUG LABEL
Date: 20141210

ACTIVE INGREDIENTS: CHELIDONIUM MAJUS 3 [hp_X]/1 mL; CHOLESTEROL 30 [hp_C]/1 mL; ARSENIC TRIOXIDE 1 [hp_M]/1 mL; ATROPA BELLADONNA 1 [hp_M]/1 mL; LYCOPODIUM CLAVATUM SPORE 1 [hp_M]/1 mL; LYCOSA TARANTULA 10 [hp_M]/1 mL
INACTIVE INGREDIENTS: WATER; ALCOHOL

DRUG FACTS:

ACTIVE INGREDIENTS:

CHELIDONIUM MAJUS 3X, CHOLESTERINUM 30C, ARSENICUM ALBUM 1M, BELLADONNA 1M, LYCOPODIUM CLAVATUM 1M, TARENTULA HISPANA 10M

INDICATIONS:

For the temporary relief of anger and rage.

WARNINGS:

If pregnant or breast-feeding, ask a health care professional before using.

Keep out of reach of children. In case of overdose, get medical help or contact a Poison Control Center right away.

Do not use if tamper evident seal is broken or missing.

Store in a cool dry place.

Keep out of reach of children. In case of overdose, get medical help or contact a Poison Control Center right away.

DIRECTIONS:

Take as directed in the Restart Program or as follows: Put 5 drops under the tongue 2x daily as needed.

Consult a physician for use in children under 12 years of age.

INDICATIONS:

For the temporary relief of anger and rage.

INACTIVE INGREDIENTS:

25% Alcohol, Demineralized water.

QUESTIONS:

MFG FOR EVOLUTION,

269 S. BEVERLY DR., 110

BEVERLY HILLS, CA 90212

www.evo-inc.com

PACKAGE LABEL DISPLAY:

HOMEOPATHIC

Liver Align

The Restart Program

5

evolution

HOLISTIC HEALTH CARE

1 fl oz (30ml)